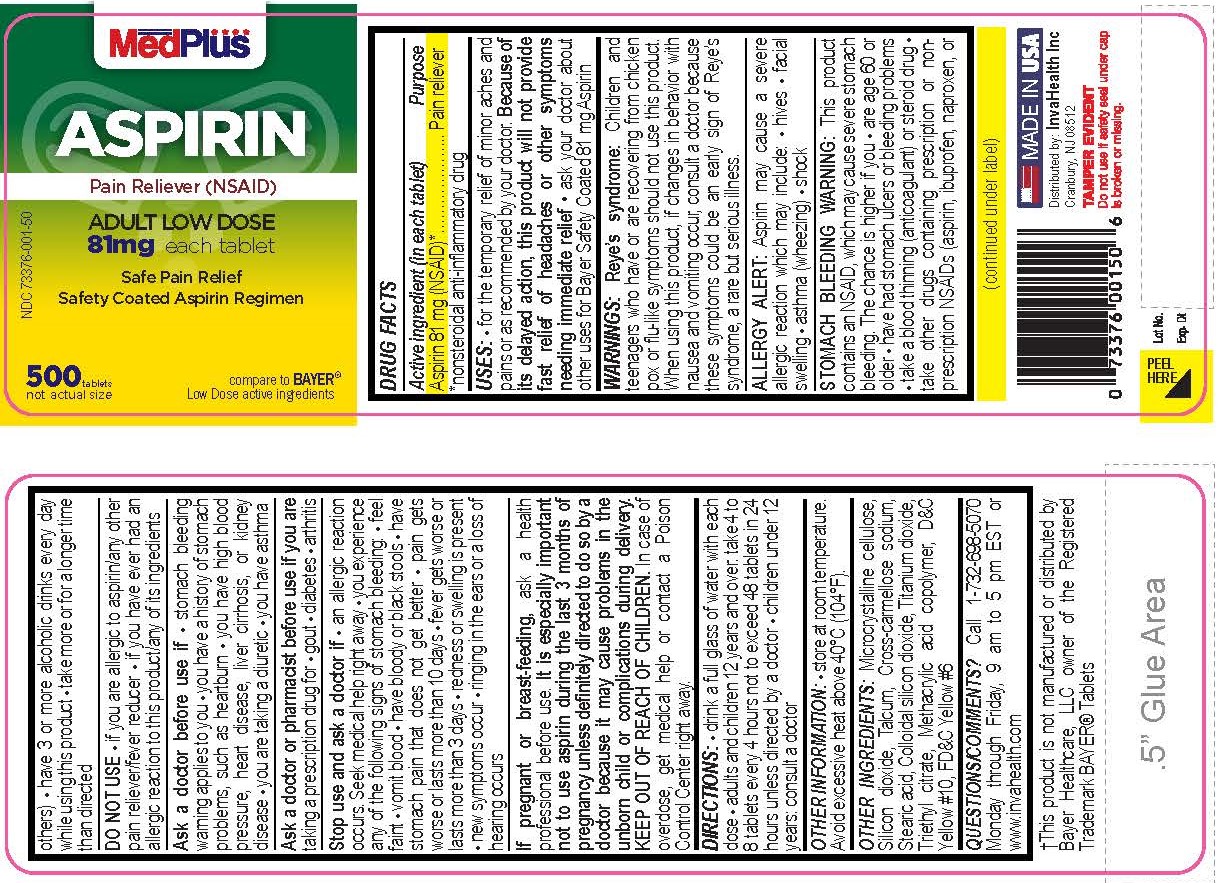 DRUG LABEL: Aspirin
NDC: 73376-001 | Form: TABLET, DELAYED RELEASE
Manufacturer: INVAHEALTH INC
Category: otc | Type: HUMAN OTC DRUG LABEL
Date: 20240108

ACTIVE INGREDIENTS: ASPIRIN 81 mg/1 1
INACTIVE INGREDIENTS: FD&C YELLOW NO. 6; STEARIC ACID; TRIETHYL CITRATE; METHACRYLIC ACID - ETHYL ACRYLATE COPOLYMER (1:2); TALC; SILICON DIOXIDE; MICROCRYSTALLINE CELLULOSE; CROSCARMELLOSE SODIUM; TITANIUM DIOXIDE; D&C YELLOW NO. 10

ACTIVE INGREDIENT

Aspirin 81 mg (NSAID*)
*nonsteroidal anti-inflammatory drug

PURPOSE

Pain reliever

WARNINGS

Reye’s syndrome:Children and teenagers who have or are recovering from chicken
pox or flu-like symptoms should not use this product. When using this product, if
changes in behavior with nausea and vomiting occur, consult a doctor because these
symptoms could be an early sign of Reye's syndrome, a rare but serious illness.
Allergy alert:Aspirin may cause a severe allergic reaction, which may include:

- hives
- facial swelling
- shock
- asthma (wheezing)

Stomach bleeding warning:This product contains an NSAID, which may cause
severe stomach bleeding. The chance is higher if you:

- are age 60 or older
- have had stomach ulcers or bleeding problem
- take a blood thinning (anticoagulant) or steroid drug
- take other drug containing prescription or nonprescription NSAIDs (aspirin,
- ibuprofen, naproxen, or others)
- have 3 or more alcoholic drinks every day while using this product
- take more or for a longer time than directed

DO NOT USE

- if you are allergic to aspirin or any other pain reliever/fever reducer
- if you have ever had an allergic reaction to this product or any of its ingredients

ASK DOCTOR

- stomach bleeding warning applies to you
- you have a history of stomach problems, such as heartburn
- you have high blood pressure, heart disease, liver cirrhosis, or kidney disease
- you are taking a diuretic
- you have asthma

ASK DOCTOR/PHARMACIST

- gout
- diabetes
- arthritis

STOP USE

an allergic reaction occurs. Seek medical help right away.
you experience any of the following signs of stomach bleeding:

- feel faint
- have bloody or black stools
- vomit blood
- have stomach pain that does not get better
- pain gets worse or lasts more than 10 days
- fever gets worse or lasts more than 3 days
- redness or swelling is present
- new symptoms occur
- ringing in the ears or a loss of hearing occurs

PREGNANCY OR BREAST FEEDING

If pregnant or breast-feeding,ask a health professional before use. It is especially
important not to use aspirin during the last 3 months of pregnancy unless
definitely directed to do so by a doctor because it may cause problems in
the unborn child or complications during delivery.

KEEP OUT OF REACH OF CHILDREN.In case of overdose, get medical help or contact a
Poison Control Center right away.

DOSAGE AND ADMINISTRATION

- drink a full glass of water with each dose
- adults and children 12 years and over: take 4 to 8 tablets every 4 hours not to

exceed 48 tablets in 24 hours unless directed by a doctor

- children under 12 years: consult a doctor

STORAGE AND HANDLING

- Store at room temprature. Avoid excessive heat above 40°C (104°F).

QUESTIONS

Call 1-609-642-6380 Monday through Friday 9 am to 5 pm EST

INACTIVE INGREDIENT

microcrystalline cellulose, colloidal silicon dioxide,
croscarmellose sodium, stearic acid, D&C yellow #10, D&C yellow #6 methacrylic
acid copolymer, talcum, titanium dioxide, triethyl citrate.

INDICATIONS AND USAGE

for the temporary relief of minor aches and pains or as recommended by your
doctor. Because of its delayed action, this product will not provide fast
relief of headaches or other symptoms needing immediate relief.
ask your doctor about other uses for Safety Coated 81 mg Aspirin

KEEP OUT OF REACH OF CHILDREN

In case of overdose, get medical help or contact a Poison Control Center right away.